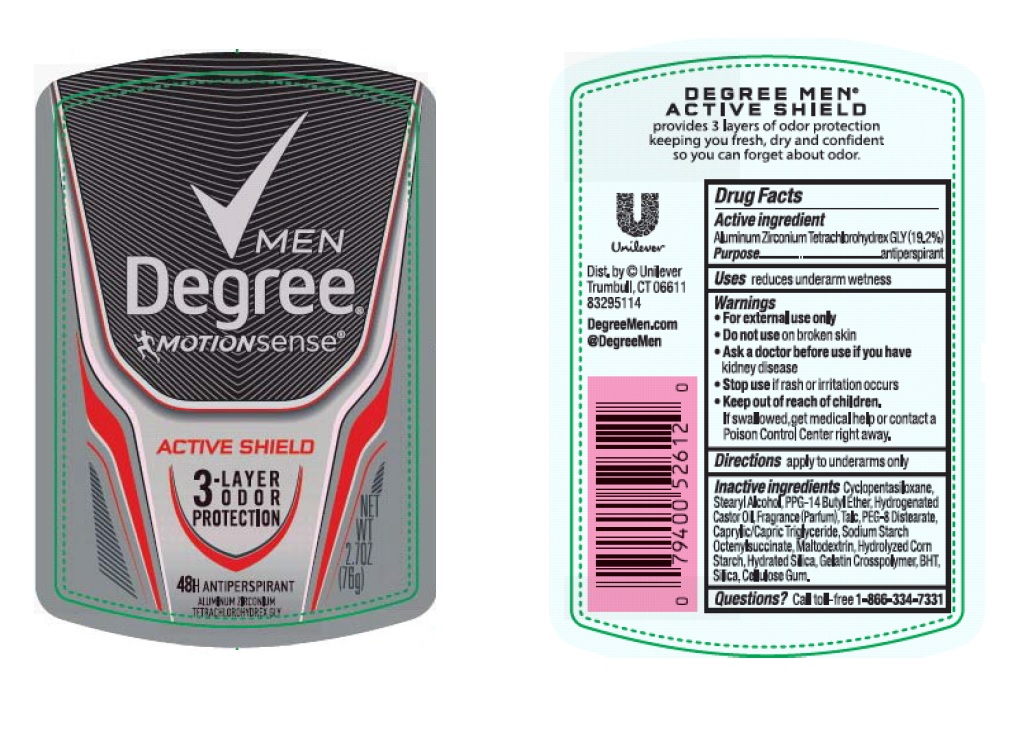 DRUG LABEL: Degree
NDC: 64942-1431 | Form: STICK
Manufacturer: Conopco Inc. d/b/a Unilever
Category: otc | Type: HUMAN OTC DRUG LABEL
Date: 20161006

ACTIVE INGREDIENTS: Aluminum Zirconium Tetrachlorohydrex GLY 19.2 g/100 g
INACTIVE INGREDIENTS: CYCLOMETHICONE 5; PPG-14 BUTYL ETHER; STEARYL ALCOHOL; HYDROGENATED CASTOR OIL; PEG-8 DISTEARATE; MEDIUM-CHAIN TRIGLYCERIDES; TALC; STARCH, CORN; BUTYLATED HYDROXYTOLUENE; HYDRATED SILICA; MALTODEXTRIN; SILICON DIOXIDE; CARBOXYMETHYLCELLULOSE SODIUM

Degree Men MotionSense Active Shield antiperspirant deodorant

Active Ingredient

Aluminum Zirconium Tetrachlorohydrex GLY (19.2%)

Purpose
anti-perspirant

Uses
reduces underarm wetness

Warnings
• For external use only

• Do not use on broken skin

• Ask a doctor before use if you have kidney disease

• Stop use if rash or irritation occurs

• Keep out of reach of children. If swallowed, get medical help or contact a Poison Control Center right away.

Directions

apply to underarms only

INACTIVE INGREDIENT

Inactive ingredients Cyclopentasiloxane, Stearyl Alcohol, PPG-14 Butyl Ether, Hydrogenated Castor Oil, Fragrance (Parfum), Talc, PEG-8 Distearate, Caprylic/Capric Triglyceride, Sodium Starch Octenylsuccinate, Hydrated Silica, Maltodextrin, Gelatin Crosspolymer, Hydrolyzed Corn Starch, BHT, Silica, Cellulose Gum

Questions?
Call toll-free 1-866-334-7331